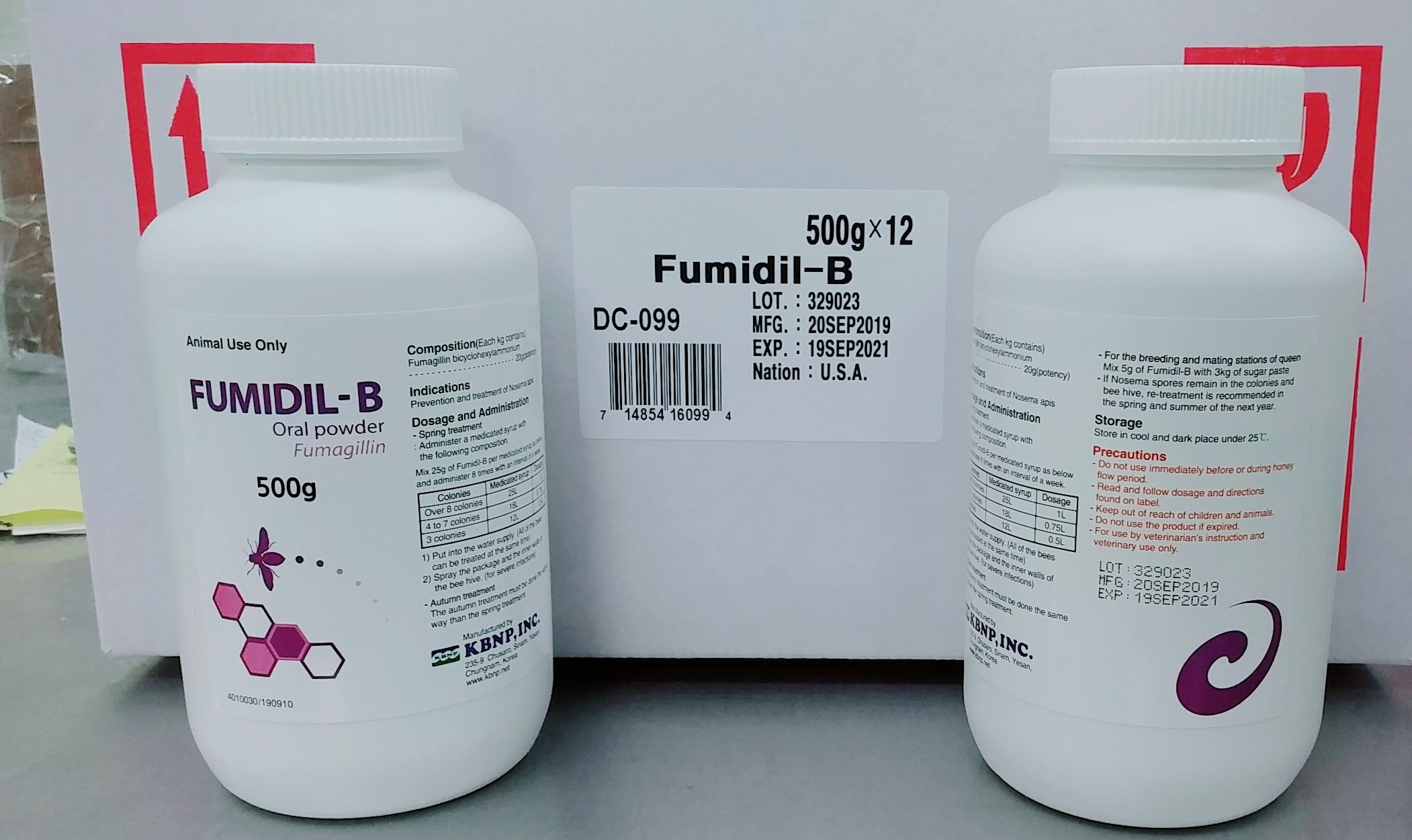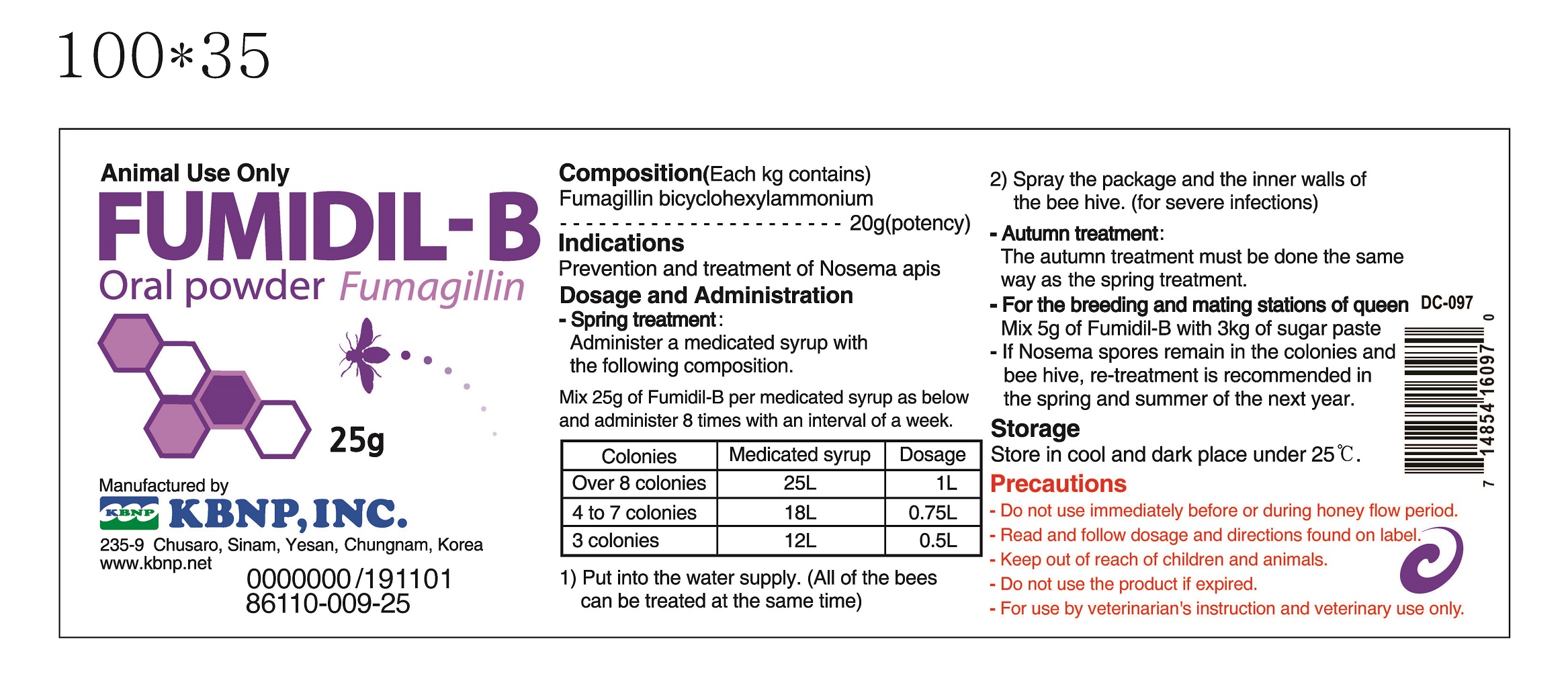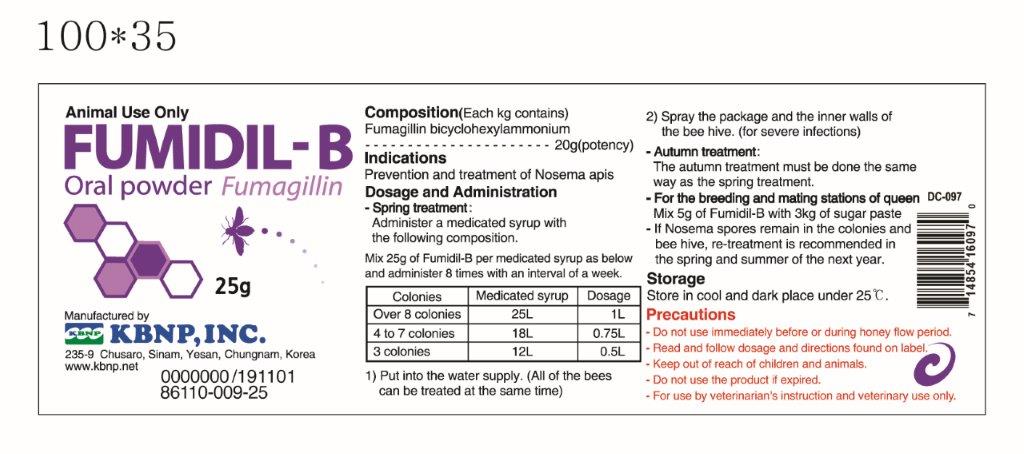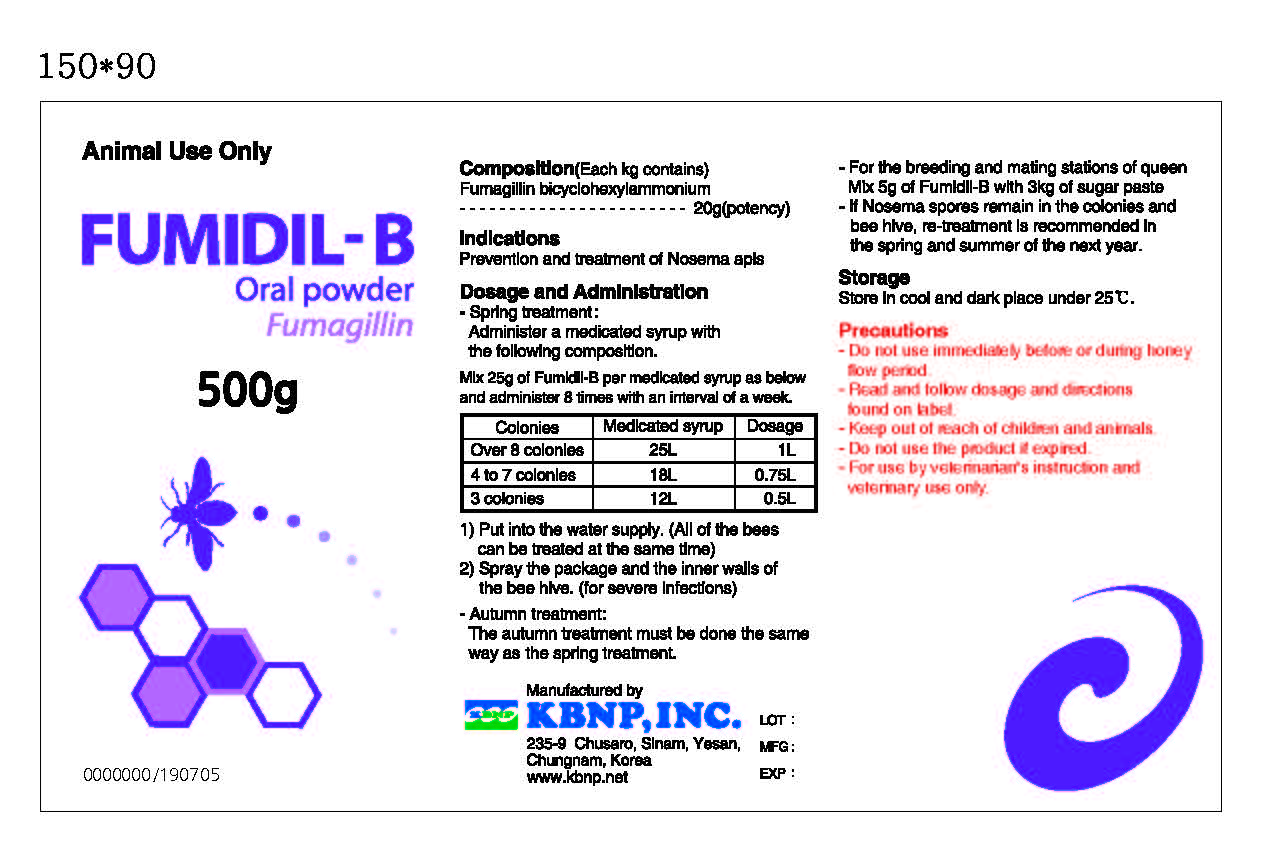 DRUG LABEL: Fumidil-B
NDC: 86110-009 | Form: POWDER
Manufacturer: KBNP, Inc
Category: animal | Type: OTC ANIMAL DRUG LABEL
Date: 20220929

ACTIVE INGREDIENTS: FUMAGILLIN 21 mg/1 g
INACTIVE INGREDIENTS: SODIUM PHOSPHATE, MONOBASIC, DIHYDRATE 489.5 mg/1 g; SODIUM PHOSPHATE, DIBASIC 489.5 mg/1 g

Product Use

Fumidil-B
Bicyclohexylammonium Fumiagillin Soluble Powder HS For Veterinary Use Only
DESCRIPTION: Fumidil-B is a water-soluble preparation containing Bicyclohexylammonium Fumagillin, equivalent to 20 mg Fumagillin base per gram of powder.

Fumidil-B has a high specific action against Nosema apis., a microscopic, single-celled parasite which causes Nosema disease in honey bees. It acts on the multiplying, disease producing parasite in the gut and is not effective against the spores. To eradicate the continuing supply of parasites, Fumidil-B must be provided over a period of several weeks.

DIRECTIONS: Fumidil-B should be dissolved in water and then added to syrup. For best results, heat the required amount of water to 95-122°F, then remove the heat source and add the Fumidil-B and the sugar in that order.
Do not add Fumidil-B to syrup over 86°F. Feed the medicated syrup within 24 hours. To prepare this concentration of medicated syrup, use the following chart.

Water +Sugar =Syrup +Fumidil-B
48.5 gallons +800.7 lbs = 110 gallons 500 gram bottle
0.44 gallons +7.3 lbs = 1 gallon 4.5 grams

Fall Feeding Medicated Syrup

2 gallons for each 2-chamber colony (approximately 30,000 bees) 1 gallon for each 1-chamber colony (approximately 12,000 bees)
¾ gallon for each 5-frame colony (approximately 12,000 bees)

Feed additional unmedicated syrup to desired colony weight for wintering.

Spring Feeding Medicated Syrup

1 gallon for each 2-chamber colony (approximately 30,000 bees)
½ gallon for each 1-chamber colony (approximately 12,000 bees)
½ gallon for each 5-frame colony (approximately 12,000 bees) 1 gallon for each package colony

Feed additional unmedicated syrup to provide nourishment until nectar is available. Each package colony is best fed Fumidil-B immediately after installation.
Colonies used for package production should be fed medicated syrup as a principle food source for one month prior to shaking for market.

Heavily infested colonies that will no longer take in syrup may be sprayed repletely, directly onto the bees, frame by frame with 1:1 sugar syrup (one-part sugar to one-part water).

WARNING:
Medicated syrup must not be fed immediately before or during the honey flow.

STORAGE INSTRUCTIONS:
Store below 77°F, protected from sunlight. Do not expose medicated syrup to sunlight.